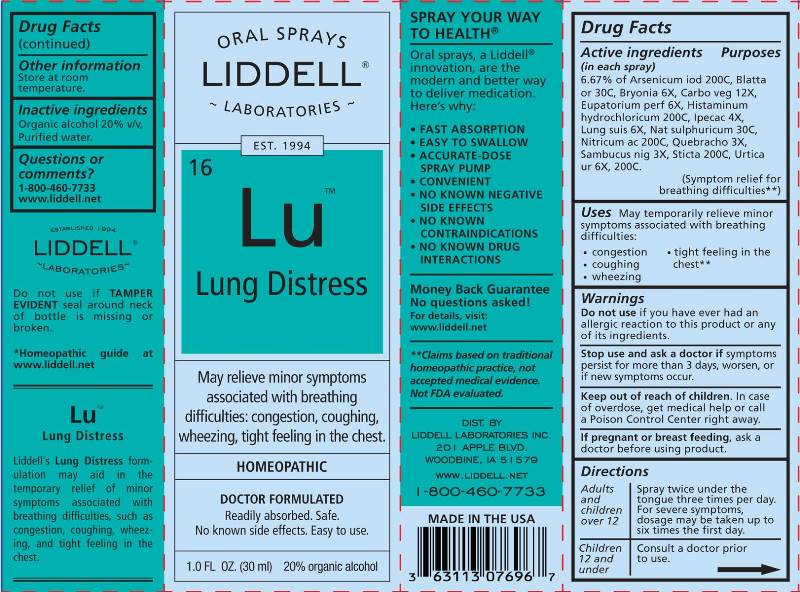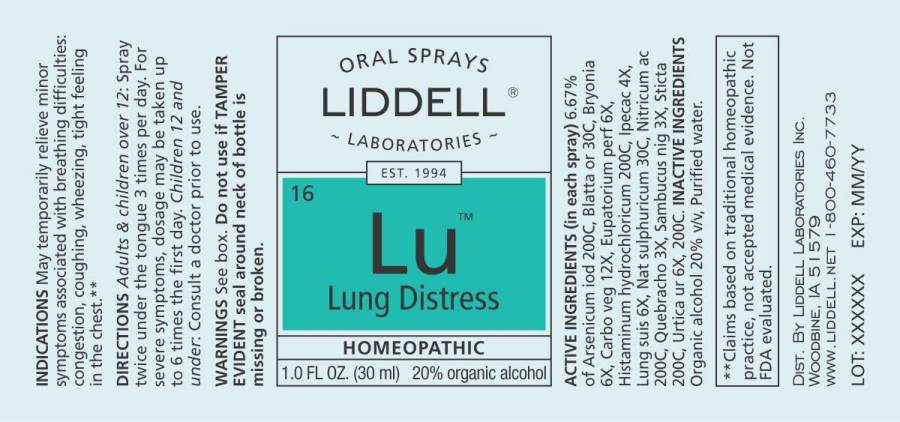 DRUG LABEL: Lung Distress
NDC: 50845-0275 | Form: SPRAY
Manufacturer: Liddell Laboratories
Category: homeopathic | Type: HUMAN OTC DRUG LABEL
Date: 20241104

ACTIVE INGREDIENTS: BLATTA ORIENTALIS 30 [hp_C]/1 mL; BRYONIA ALBA ROOT 6 [hp_X]/1 mL; ACTIVATED CHARCOAL 12 [hp_X]/1 mL; EUPATORIUM PERFOLIATUM FLOWERING TOP 6 [hp_X]/1 mL; HISTAMINE DIHYDROCHLORIDE 200 [hp_C]/1 mL; IODINE 200 [hp_C]/1 mL; IPECAC 4 [hp_X]/1 mL; SUS SCROFA LUNG 6 [hp_X]/1 mL; SODIUM SULFATE 30 [hp_C]/1 mL; NITRIC ACID 200 [hp_C]/1 mL; PULSATILLA PRATENSIS WHOLE 30 [hp_C]/1 mL; ASPIDOSPERMA QUEBRACHO-BLANCO BARK 12 [hp_X]/1 mL; SAMBUCUS NIGRA FLOWERING TOP 3 [hp_X]/1 mL; LOBARIA PULMONARIA 200 [hp_C]/1 mL; URTICA URENS WHOLE 6 [hp_X]/1 mL
INACTIVE INGREDIENTS: WATER; ALCOHOL

DRUG FACTS:

ACTIVE INGREDIENTS:

(in each spray) 6.25% of Blatta Orientalis 30C, Bryonia 6X, Carbo Vegetabilis 12X, Eupatorium Perfoliatum 6X, Histaminum Hydrochloricum 200C, Iodium 200C, Ipecacuanha 4X, Lung Suis 6X, Natrum Sulphuricum 30C, Nitricum Acidum 200C, Pulsatilla (Pratensis) 30C, Quebracho 12X, Sambucus Nigra 3X, Sticta Pulmonaria 200C, Urtica Urens 6X, 200C.

USES:

May temporarily relieve minor symptoms associated with breathing difficulties:

• congestion
• coughing
• wheezing
• tight feeling in the chest**

**Claims based on traditional homeopathic practice, not accepted medical evidence. Not FDA evaluated.

WARNINGS:

Do not use if you have ever had an allergic reaction to this product or any of its ingredients.

Stop use and ask a doctor if symptoms persist for more that 3 days, worsen, or if new symptoms occur.

Keep out of reach of children. In case of overdose, get medical help or call a Poison Control Center right away.

If pregnant or breast-feeding, ask a health professional before use.

OTHER INFORMATION: Store at room temperature.

Do not use if TAMPER EVIDENT seal around neck of bottle is missing or broken.

Keep out of reach of children. In case of overdose, get medical help or call a Poison Control Center right away.

DIRECTIONS:

Adults and children over 12: Spray twice under the tongue 3 times per day. For frequent symptoms, dosage may be taken up to six times the first day.

Children 12 and under: Consult a doctor prior to use.

INDICATIONS:

May temporarily relieve minor symptoms associated with breathing difficulties:

• congestion
• coughing
• wheezing
• tight feeling in the chest**

**Claims based on traditional homeopathic practice, not accepted medical evidence. Not FDA evaluated.

INACTIVE INGREDIENTS:

Organic alcohol 20% v/v, Purified water.

QUESTIONS:

DIST. BY:

LIDDELL LABORATORIES INC.

201 APPLE BLVD.

WOODBINE, IA 51579

WWW.LIDDELL.NET

1-800-460-7733

PACKAGE LABEL DISPLAY:

ORAL SPRAYS

LIDDELL
LABORATORIES

EST 1994

16 Lu
Lung Distress

May relieve minor symptoms

associated with breathing

difficulties: congestion, coughing,

wheezing, tight feeling in the chest.

HOMEOPATHIC

DOCTOR FORMULATED

Readily absorbed. Safe.
No known side effects. Easy to use.

1.0 FL OZ. (30 ml)